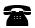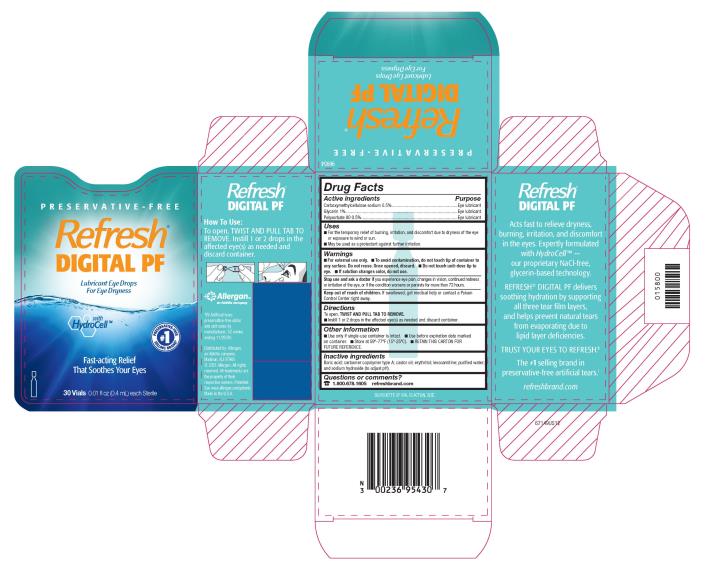 DRUG LABEL: Refresh Digital PF
NDC: 0023-6954 | Form: SOLUTION/ DROPS
Manufacturer: Allergan, Inc.
Category: otc | Type: HUMAN OTC DRUG LABEL
Date: 20221128

ACTIVE INGREDIENTS: CARBOXYMETHYLCELLULOSE SODIUM 5 mg/1 mL; GLYCERIN 10 mg/1 mL; POLYSORBATE 80 5 mg/1 mL
INACTIVE INGREDIENTS: BORIC ACID; CARBOMER COPOLYMER TYPE A; CASTOR OIL; ERYTHRITOL; LEVOCARNITINE; WATER; SODIUM HYDROXIDE

REFRESH® DIGITAL PRESERVATIVE-FREE
Drug Facts

Active ingredients

Carboxymethylcellulose sodium 0.5%

Glycerin 1%

Polysorbate 80 0.5%

Purpose

Eye lubricant

Eye lubricant

Eye lubricant

Uses

- For the temporary relief of burning, irritation, and discomfort due to dryness of the eye or exposure to wind or sun.
- May be used as a protectant against further irritation.

Warnings

- For external use only.
- To avoid contamination, do not touch tip of container to any surface. Do not reuse. Once opened, discard.
- Do not touch unit-dose tip to eye.
- If solution changes color, do not use.

Stop use and ask a doctor

if you experience eye pain, changes in vision, continued redness or irritation of the eye, or if the condition worsens or persists for more than 72 hours.

Keep out of reach of children.

If swallowed, get medical help or contact a Poison Control Center right away.

Directions

To open, TWIST AND PULL TAB TO REMOVE. Instill 1 or 2 drops in the affected eye(s) as needed and discard container.

Other information

- Use only if single-use container is intact.
- Use before expiration date marked on container.
- Store at 59°-77°F (15°-25°C).
- RETAIN THIS CARTON FOR FUTURE REFERENCE.

Inactive ingredients

Boric acid; carbomer copolymer type A; castor oil; erythritol; levocarnitine; purified water; and sodium hydroxide (to adjust pH).

Questions or comments?

1.800.678.1605

refreshbrand.com

v1.0DFL6954

Principal Display Panel

NDC 0023-6954-30

Refresh®
DIGITAL PF
Lubricant Eye Drops
For Eye Dryness
with HydroCell™
Fast-acting Relief
That Soothes Your Eyes
30 Vials (0.01 fl oz (0.4 mL) each Sterile